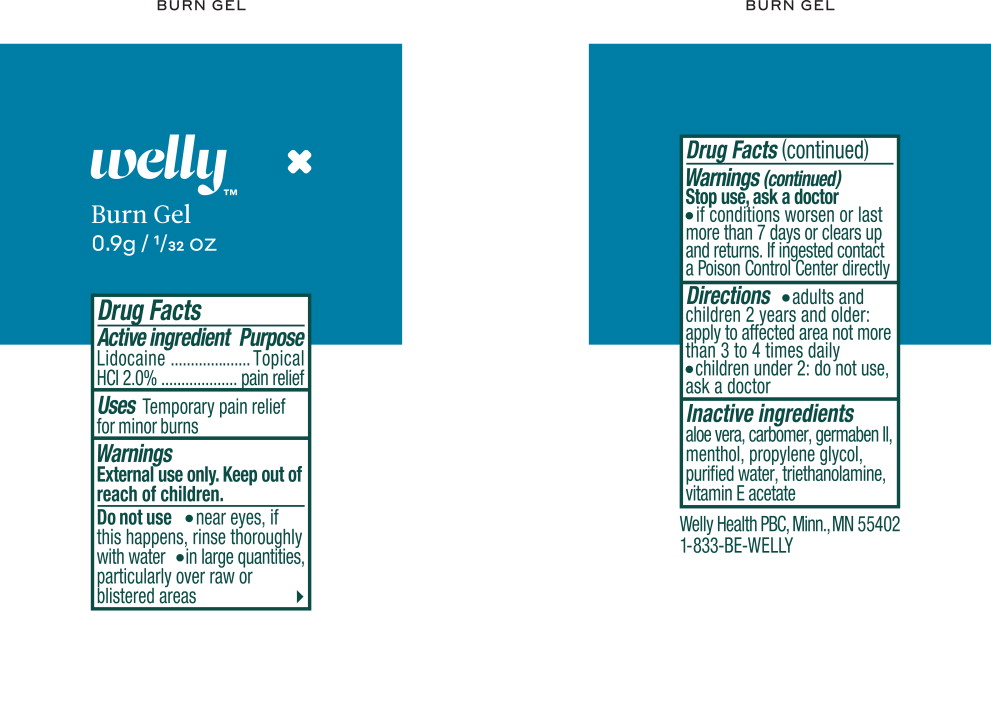 DRUG LABEL: Analgesic
NDC: 72663-500 | Form: GEL
Manufacturer: Welly Health PBC
Category: otc | Type: HUMAN OTC DRUG LABEL
Date: 20190225

ACTIVE INGREDIENTS: lidocaine hydrochloride 2 g/1 mL
INACTIVE INGREDIENTS: aloe vera leaf; carboxypolymethylene; diazolidinyl urea; menthol, unspecified form; propylene glycol; water; trolamine; .alpha.-tocopherol, d-

Drug Facts

Active ingredient

Lidocaine

HCl 2.0%

Purpose

Topical

pain relief

Uses

Temporary pain relief for minor burns

Warnings

KEEP OUT OF REACH OF CHILDREN

External use only. Keep out of reach of children.

Do not use

- near eyes, if this happens, rinse thoroughly with water
- in large quantities, particularly over raw or blistered areas

Stop use, ask a doctor

- if conditions worsen or last more than 7 days or clears up and returns. If ingested contact a Poison Control Center directly

Directions

- adults and children 2 years and older: apply to affected area not more than 3 to 4 times daily
- children under 2: do not use, ask a doctor

Inactive ingredients

aloe vera, carbomer, germaben II, menthol, propylene glycol, purified water, triethanolamine, vitamin E acetate

Welly Health PBC, Minn., MN 55402

1-833-BE-WELLY

Principal Display Panel - Welly Health Burn Gel Pouch Label

Welly™

Burn Gel

0.9/ 1/32 OZ